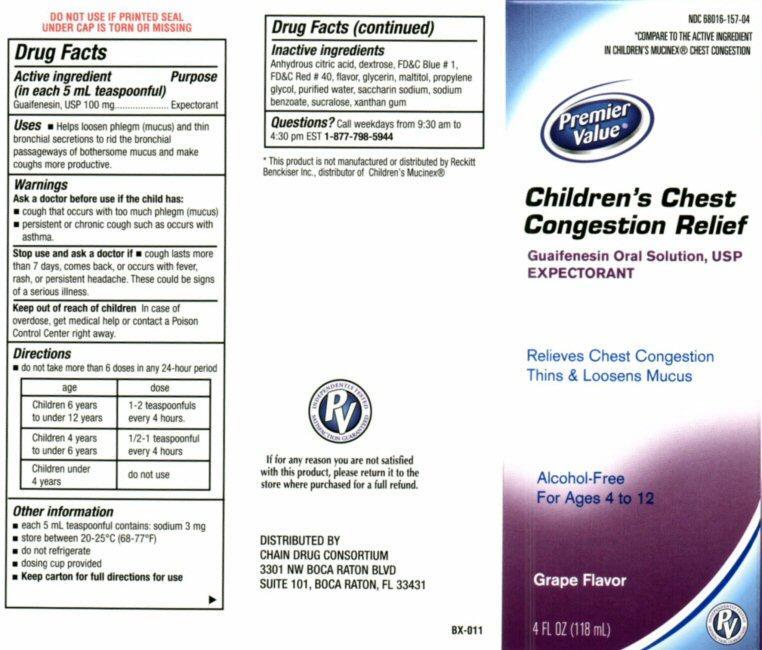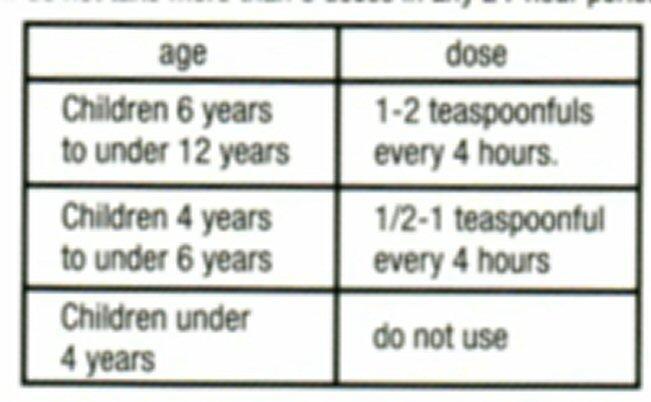 DRUG LABEL: Childrens Chest Congestion Relief
NDC: 68016-157 | Form: LIQUID
Manufacturer: Chain Drug Consortium, LLC
Category: otc | Type: HUMAN OTC DRUG LABEL
Date: 20130401

ACTIVE INGREDIENTS: GUAIFENESIN 100 mg/5 mL
INACTIVE INGREDIENTS: ANHYDROUS CITRIC ACID; DEXTROSE; FD&C BLUE NO. 1; FD&C RED NO. 40; GLYCERIN; MALTITOL; PROPYLENE GLYCOL; WATER; SACCHARIN SODIUM; SODIUM BENZOATE; SUCRALOSE; XANTHAN GUM

Active ingredient

Drug Facts
Active ingredient (in each 5 mL teaspoonful)
Guaifenesin, USP 100 mg

Purpose

Expectorant

Keep out of reach of children

In case of overdose, get medical help or contact a Poison Control center right away.

Uses

- Helps loosen phlegm (mucus) and thin bronchial secretions to rid the bronchial passageways of bothersome mucus and makes coughs more productive.

Warnings

Ask a doctor before use if the child has:

- cough that occurs with too much phlegm (mucus)
- persistent or chronic cough such as occurs with asthma

Stop use and ask a doctor if

- cough lasts more than 7 days, comes back or occurs with fever, rash, or persistent headache.
- These could be signs of a serious condition.

Directions

- do not take more than 6 doses in any 24-hour period

Other information

- each 5 mL teaspoon contains: sodium 3 mg
- store between 20-25 ° C (68-77° F)
- do not refrigerate
- dosage cup provided
- Keep carton for full directions for use

Inactive ingredients

citric acid anhydrous, dextrose, FD and C Blue # 1, FD and C Red # 40, flavors, glycerin, maltitol, propylene glycol, purified water, saccharin sodium, sodium benzoate, sucralose, xanthan gum

Questions?

Call weekdays from 9:30 AM to 4:30 PM EST
1-877-798-5944

Product Label

NDC 68016-157-04
*COMPARE TO THE ACTIVE INGREDIENTS IN CHILDRENS MUCINEX® CHEST CONGESTION
Premier Value®
Childrens Chest Congestion Relief
Guaifenesin Oral Solution, USP
EXPECTORANT
Relieves Chest Congestion
Thins and Loosens Mucus
Alcohol-Free
For Ages 4 to 12
Grape Flavor
4 FL OZ (118mL)
INDEPENDENTLY TESTED SATISFACTION GUARANTEED PV
DO NOT USE IF PRINTED SEAL UNDER CAP IS TORN OR MISSING
*This product is not manufactured or distributed by Reckitt Benckiser Inc. distributor of Childrens Mucinex®
If for Any reason you are not satisfied with this product, please return it to the store where purchased for a full refund.
DISTRIBUTED BY
CHAIN DRUG CONSORTIUM
3301 NW BOCA RATON BLVD
SUITE 101, BOCA RATON, FL 33431
BX-011